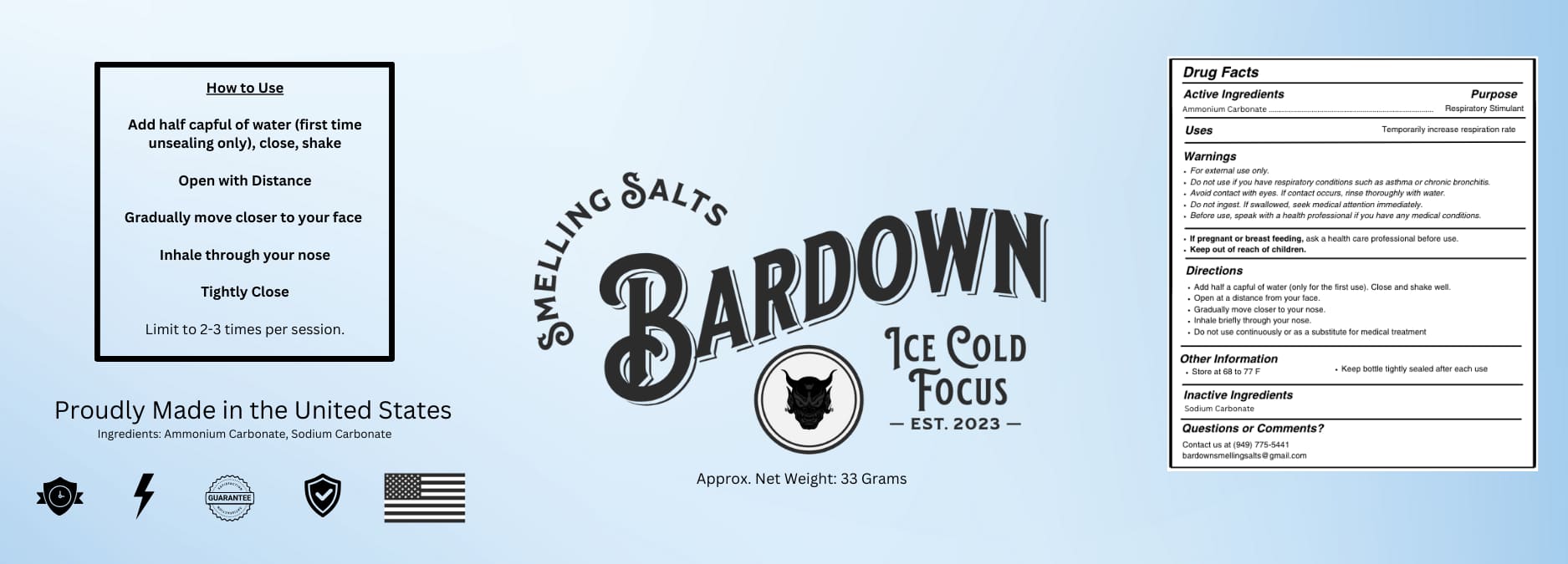 DRUG LABEL: Bardown Smelling Salts
NDC: 85263-112 | Form: POWDER
Manufacturer: TRGResearch LLC
Category: otc | Type: HUMAN OTC DRUG LABEL
Date: 20250416

ACTIVE INGREDIENTS: AMMONIUM CARBONATE 25 g/33 g
INACTIVE INGREDIENTS: SODIUM CARBONATE

TRGResearch LLC Ammonia Inhalant

Purpose

Respirator/ Stimulant

Use

Temporarily increase respiration rate

WARNINGS

For external use only.

Do not use it if you have respiratory conditions such as asthma or chronic bronchitis.

Avoid contact with eyes. If contact occurs, Anse thoroughly with water.

Do not ingest. If swallowed, seek medical attention immediately.

Before use, speak with a health professional if you have any medical concfilione.

If pregnant or breastfeeding, ask a health care professional before use. Keep out of reach of children.

Keep out of reach of children.

Directions

Add half a capful of water (only for the first use). Close and shake well.

Open at a distance from your face.

Gradually move closer to your nose.

Male Welly through your nose.

Do not use continuously or as a substitute for medical treatment.

OTHER SAFETY INFORMATION

Store at 68 to 77 F

Keep the bottle tightly sealed after each use

Questions or Comments? Contact us at (949) 775-5441 bardownsmellingsaltsegmail.com

Inactive ingredients

Sodium Carbonate